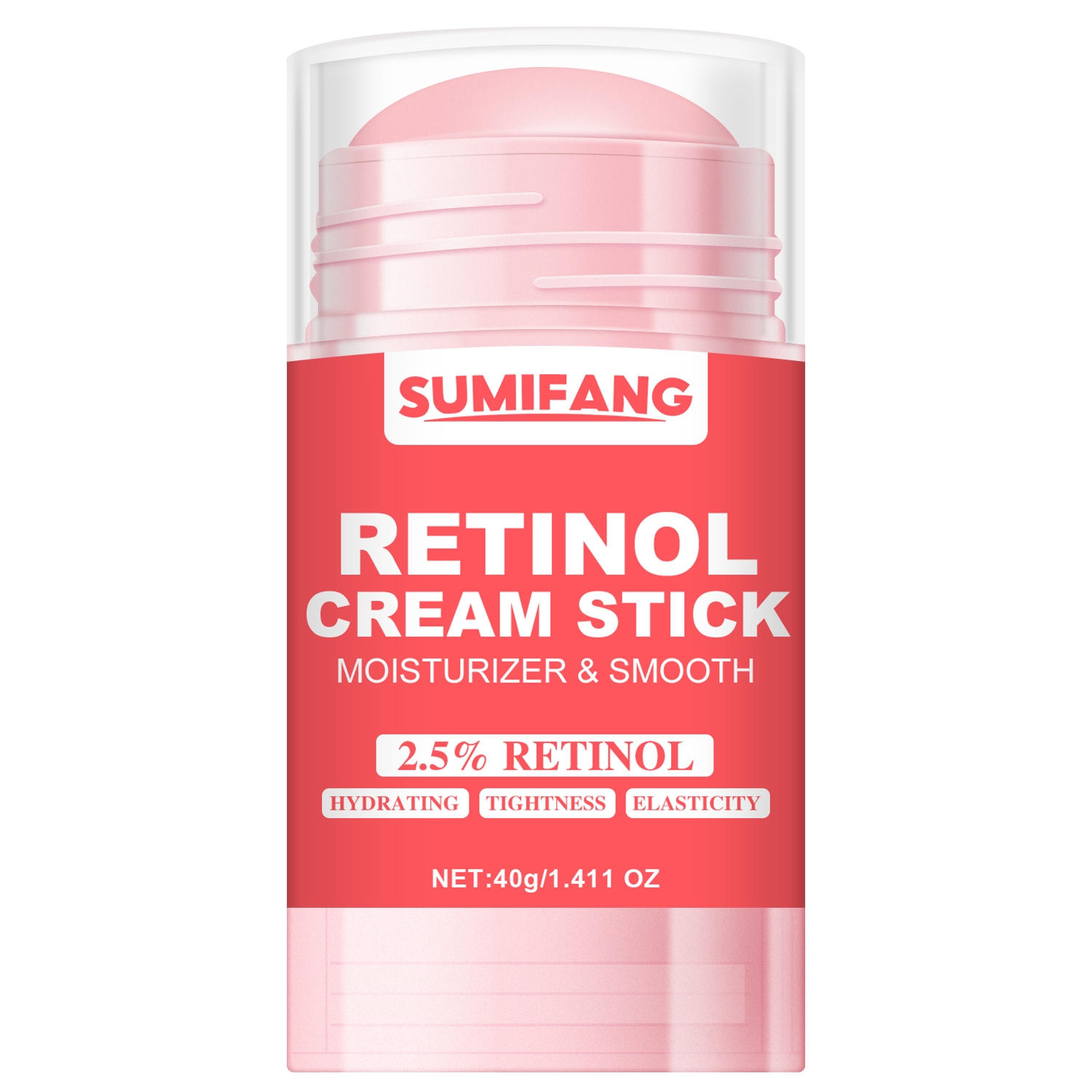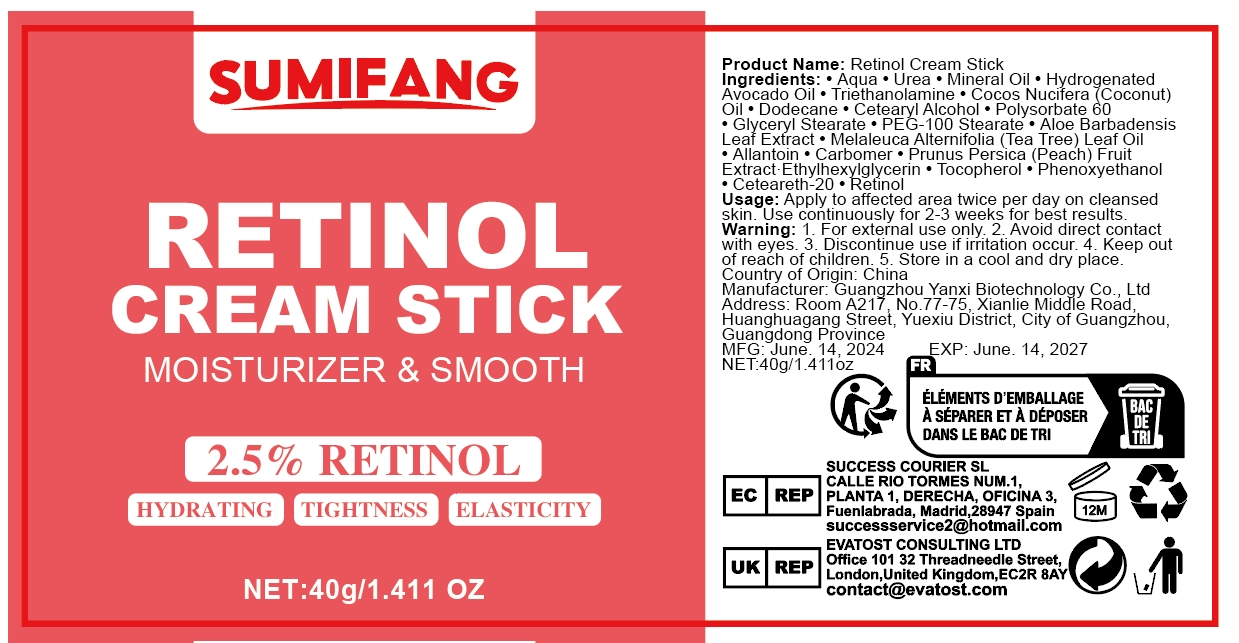 DRUG LABEL: Retinol CreamStick
NDC: 84025-096 | Form: STICK
Manufacturer: Guangzhou Yanxi Biotechnology Co.. Ltd
Category: otc | Type: HUMAN OTC DRUG LABEL
Date: 20240729

ACTIVE INGREDIENTS: RETINOL 5 mg/40 g; MINERAL OIL 3 mg/40 g
INACTIVE INGREDIENTS: WATER

DOSAGE AND ADMINISTRATION

Cream stick for daily moisturizing of facial skin

WARNINGS

keep out of children

INACTIVE INGREDIENT

Aqua

INDICATIONS AND USAGE

For moisturizing facial skin

Keep out of children

PURPOSE

Moisturizing Treatment for Facial Skin